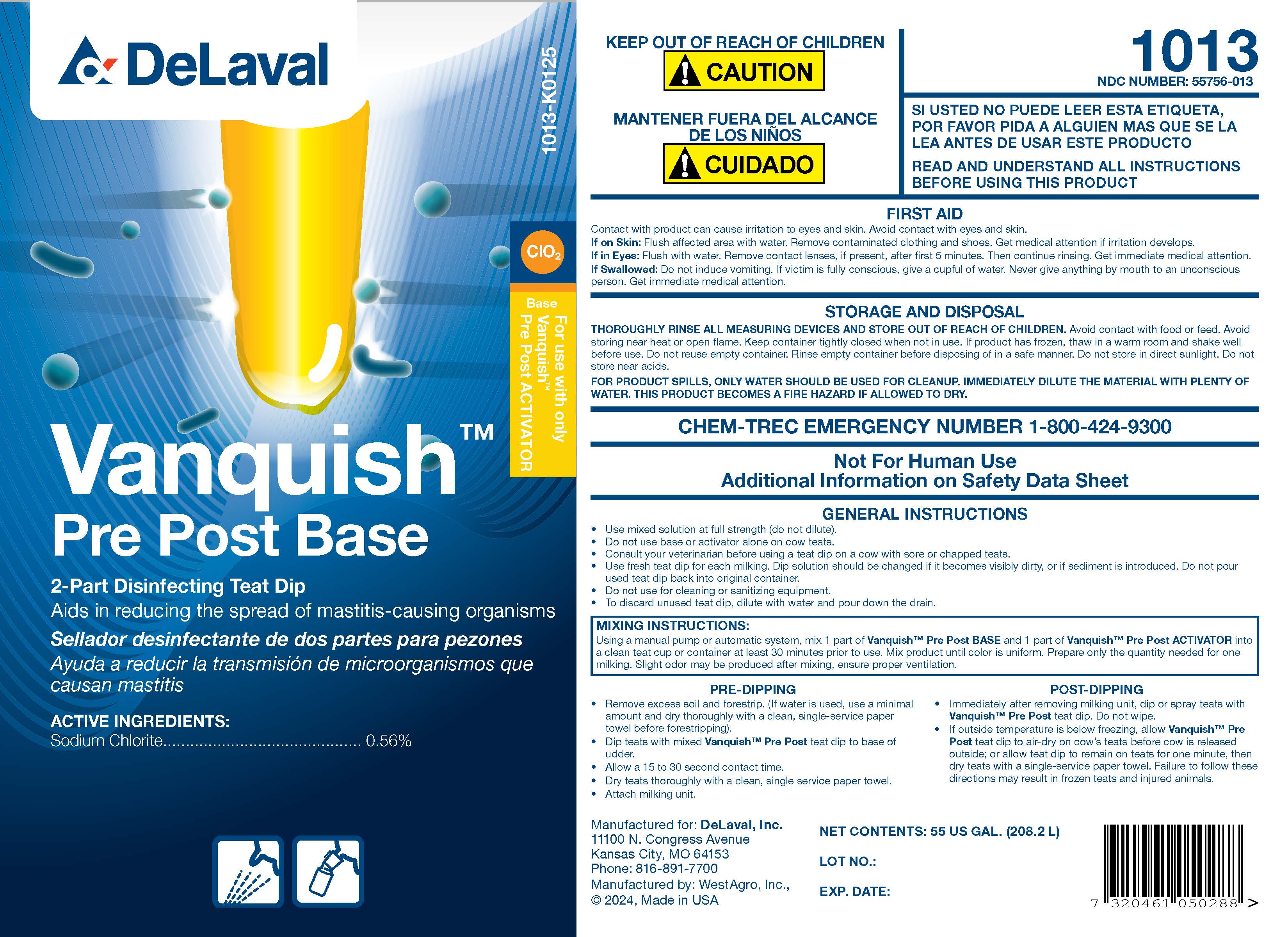 DRUG LABEL: Vanquish Pre-Post Base
NDC: 55756-013 | Form: SOLUTION
Manufacturer: DeLaval Inc.
Category: animal | Type: OTC ANIMAL DRUG LABEL
Date: 20250225

ACTIVE INGREDIENTS: Sodium Chlorite 7.0 g/1 L

DeLaval
VanquishTM
Pre Post Base

PURPOSE

2-Part Disinfecting Teat Dip
Aids in reducing the spread of mastitis-causing organisms

Sanitizante pre y post ordeno
Ayuda a reducir la transmision de microorganismos que causan mastitis

ACTIVE INGREDIENTS:

Sodium Chlorite .................. 0.56%

Base

For use with only VanquishTM Pre Post ACTIVATOR

KEEP OUT OF REACH OF CHILDREN

! CAUTION

MANTENER FUERA DEL ALCANCE DE LOS NINOS

! CUIDADO

1013

NDC 55756-013

SI USTED NO PUEDE LEER ESTA ETIQUETA, POR FAVOR PIDA A ALGUIEN MAS QUE SE LA LEA ANTES DE USAR ESTE PRODUCTO

READ AND UNDERSTAND ALL INSTRUCTIONS BEFORE USING THIS PRODUCT

FIRST AID
Contact with product can cause irritation to eyes and skin. Avoid contact with eyes and skin.

If On Skin: Flush affected area with water. Remove contaminated clothing and shoes. Get medical attention if irritation develops.

If in Eyes: Flush with water. Remove contact lenses, if present, after first 5 minutes. Then continue rinsing. Get immediate medical attention.

If Swallowed: Do not induce vomiting. If victim is fully conscious, give a cupful of water. Never give anything by mouth to an unconscious person. Get immediate medical attention.

STORAGE AND DISPOSAL
THOROUGHLY RINSE ALL MEASURING DEVICES AND STORE OUT OF REACH OF CHILDREN. Avoid contact with food or feed. Avoid storing near heat or open flame. Keep container tightly closed when not in use. If product has frozen, thaw in a warm room and shake well before use. Do not reuse empty container. Rinse empty container before disposing of in a safe manner. Do not store in direct sunlight. Do not store near acids.

FOR PRODUCT SPILLS, ONLY WATER SHOULD BE USED FOR CLEANUP. IMMEDIATELY DILUTE THE MATERIAL WITH PLENTY OF WATER. THIS PRODUCT BECOMES A FIRE HAZARD IF ALLOWED TO DRY.

CHEM-TREC EMERGENCY NUMBER 1-800-424-9300

Not for Human Use

Additional Information on Safety Data Sheet

DOSAGE AND ADMINISTRATION

GENERAL INSTRUCTIONS

- Use mixed solution at full strength (do not dilute).
- Do not use base or activator alone on cow teats.
- Consult your veterinarian before using a teat dip on a cow with sore or chapped teats.
- Use fresh teat dip for each milking. Dip solution should be changed if it becomes visibly dirty, or if sediment is introduced. Do not pour used teat dip back into original container.
- Do not use for cleaning or sanitizing equipment.
- To discard unused teat dip, dilute with water and pour down the drain.

MIXING INSTRUCTIONS
Using a manual pump or automatic system, mix 1 part of VanquishTM Pre Post BASE and 1 part of VanquishTM Pre Post ACTIVATOR into a clean teat cup or container at least 30 minutes prior to use. Mix product until color is uniform. Prepare only the quantity needed for one milking. Slight odor may be produced after mixing, ensure proper ventilation.

PRE-DIPPING

- Remove excess soil and forestrip. (If water is used, use a minimal amount and dry thoroughly with a clean, single-service paper towel before forestripping).
- Dip teats with mixed VanquishTM Pre Post teat dip to base of udder.
- Allow a 15 to 30 second contact time.
- Dry teats thoroughly with a clean, single service paper towel.
- Attach milking unit.

POST-DIPPING

- Immediately after removing milking unit, dip or spray teats with VanquishTM Pre Post teat dip. Do not wipe.
- If outside temperature is below freezing, allow VanquishTM Pre Post teat dip to air-dry on cow's teats before cow is released outside; or allow teat dip to remain on teats for one minute, then dry teats with a single-service paper towel. Failure to follow these directions may result in frozen teats and injured animals.

Manufactured for: DeLaval, Inc.
11100 N. Congress Avenue
Kansas City, MO 64153
Phone: 816-891-7700
Manufactured by: WestAgro, Inc.,
©2024, Made in USA

NET CONTENTS: US Gal. (L)

LOT NO.:

EXP. DATE:

PACKAGE LABEL

Add image transcription here...